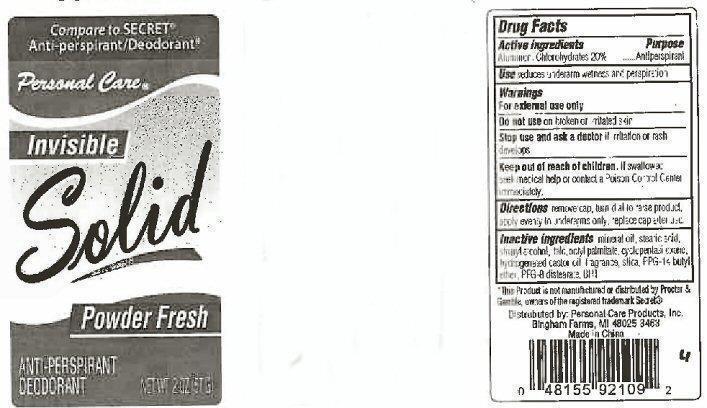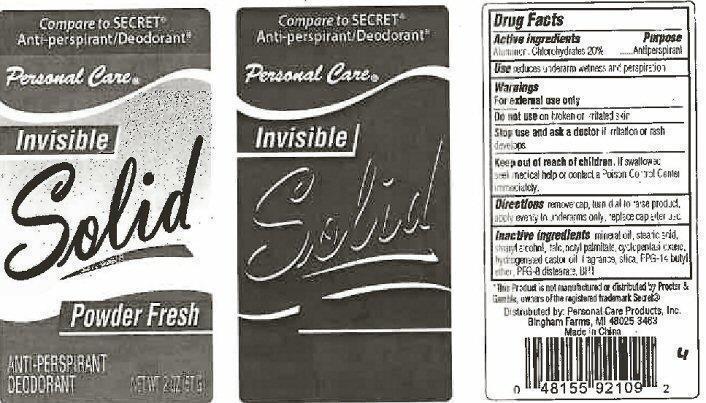 DRUG LABEL: Solid anti perspirant
                        
                
                
NDC: 29500-9210 | Form: CREAM
Manufacturer: Personal Care Products
Category: otc | Type: HUMAN OTC DRUG LABEL
Date: 20130916

ACTIVE INGREDIENTS: ALUMINUM CHLOROHYDRATE 11.4 g/57 g
INACTIVE INGREDIENTS: MINERAL OIL; STEARIC ACID; STEARYL ALCOHOL; TALC; ETHYLHEXYL PALMITATE; CYCLOMETHICONE 5; HYDROGENATED CASTOR OIL; PPG-14 BUTYL ETHER; PEG-8 DISTEARATE; BUTYLATED HYDROXYTOLUENE

Solid Powder fresh anti perspirant deodorant

Active Ingredients

Alluminum Chlorohydrates 20%

PURPOSE

Antiperspirant

Keep out of reach of children. If swallowed, seek medical help or contact a Poison Control Center immediately.

INDICATIONS AND USAGE

Use- reduces underarm wetness and perspiration.

Warnings

For external use only

Do not use on broken or irritated skin

Stop use and ask a doctor if irritation or rash develops.

DOSAGE AND ADMINISTRATION

Directions remove cap, turn dial to raise product, apply evenly to underarms only, replace cap after use.

INACTIVE INGREDIENT

Inactive ingredients mineral oil, stearic acid, stearyl alcohol, talc, octyl palmitate, cyclopentasiloxane, hydrogenated castor oil, fragrance, slica, PPG-14 butyl ether, PEG-8 distearate, BHT

PACKAGE LABEL

compare to secret antiperspirant/deodorant

Personal Care

Invisible Solid

Powder Fresh

Anti perspirant Deodorant

net wt 2 oz (57 G)